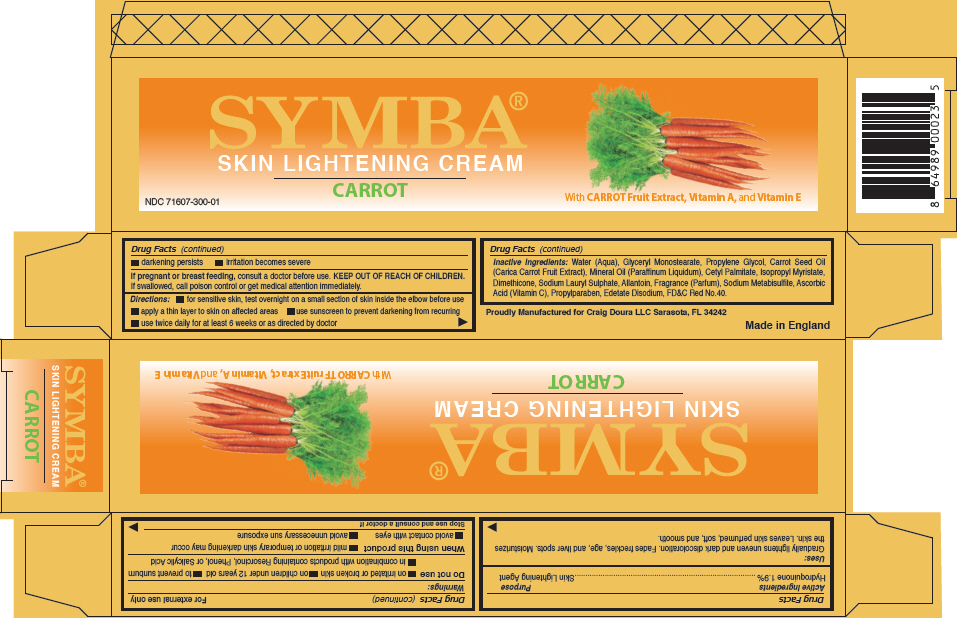 DRUG LABEL: SYMBA Skin Lightening
NDC: 71607-300 | Form: CREAM
Manufacturer: Craig Doura LLC
Category: otc | Type: HUMAN OTC DRUG LABEL
Date: 20171228

ACTIVE INGREDIENTS: HYDROQUINONE 19 mg/1 g
INACTIVE INGREDIENTS: Water; Glyceryl Monostearate; Propylene Glycol; CARROT SEED OIL; Mineral Oil; Cetyl Palmitate; Isopropyl Myristate; Dimethicone; Sodium Lauryl Sulfate; Allantoin; Sodium Metabisulfite; Ascorbic Acid; Propylparaben; Edetate Disodium; FD&C Red No. 40

SYMBA® Skin Lightening

Drug Facts

Active Ingredients

Hydroquinone 1.9%

Purpose

Skin Lightening Agent

Uses

Gradually lightens uneven and dark discoloration. Fades freckles, age, and liver spots. Moisturizes the skin. Leaves skin perfumed, soft, and smooth.

For external use only

Warnings

Do not use

- on irritated or broken skin
- on children under 12 years old
- to prevent sunburn
- in combination with products containing Resorcinol, Phenol, or Salicylic Acid

When using this product

- mild irritation or temporary skin darkening may occur
- avoid contact with eyes
- avoid unnecessary sun exposure

Stop use and consult a doctor if

- darkening persists
- irritation becomes severe

PREGNANCY OR BREAST FEEDING

If pregnant or breast feeding, consult a doctor before use.

KEEP OUT OF REACH OF CHILDREN. If swallowed, call poison control or get medical attention immediately.

Directions

- for sensitive skin, test overnight on a small section of skin inside the elbow before use
- apply a thin layer to skin on affected areas
- use sunscreen to prevent darkening from recurring
- use twice daily for at least 6 weeks or as directed by doctor

Inactive Ingredients

Water (Aqua), Glyceryl Monostearate, Propylene Glycol, Carrot Seed Oil (Carica Carrot Fruit Extract), Mineral Oil (Paraffinum Liquidum), Cetyl Palmitate, Isopropyl Myristate, Dimethicone, Sodium Lauryl Sulphate, Allantoin, Fragrance (Parfum), Sodium Metabisulfite, Ascorbic Acid (Vitamin C), Propylparaben, Edetate Disodium, FD&C Red No.40.

PRINCIPAL DISPLAY PANEL - 57 g Tube Carton

SYMBA®
SKIN LIGHTENING CREAM

CARROT

With CARROT Fruit Extract, Vitamin A, and Vitamin E

NDC 71607-300-01